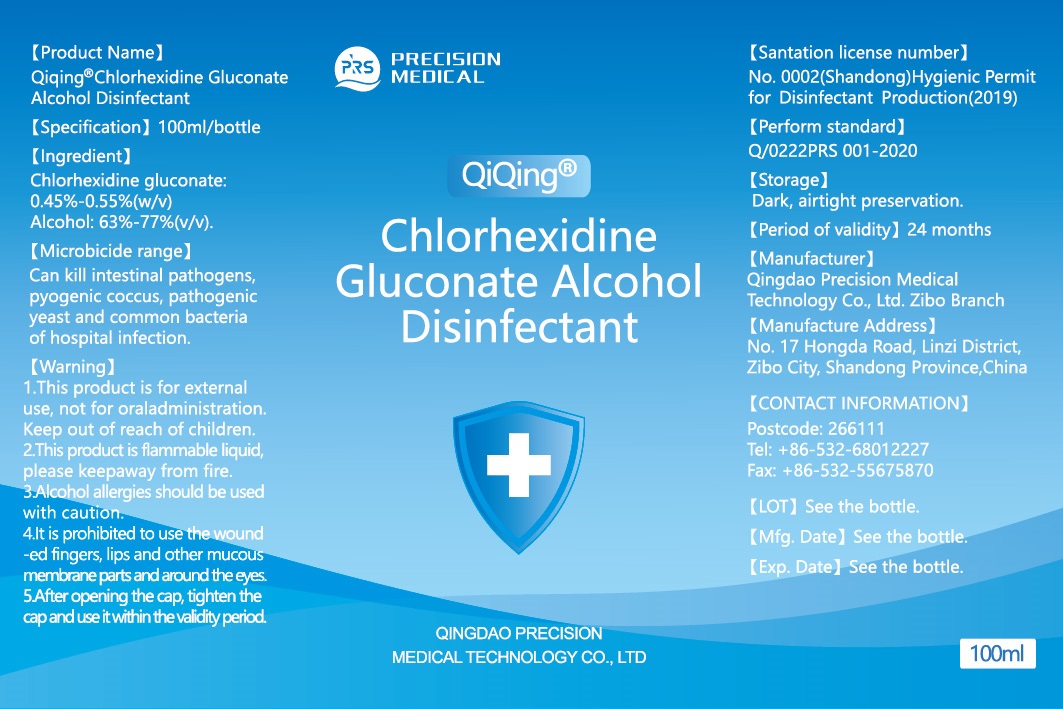 DRUG LABEL: (Qiqing) Chlorhexidine Gluconate Alcohol Disinfectant
NDC: 77919-001 | Form: LIQUID
Manufacturer: Qingdao precision medical technology co., LTD. Zibo branch
Category: otc | Type: HUMAN OTC DRUG LABEL
Date: 20200515

ACTIVE INGREDIENTS: CHLORHEXIDINE GLUCONATE 0.45 mg/100 mL; ALCOHOL 75 mL/100 mL
INACTIVE INGREDIENTS: GLYCERIN 1.45 mL/100 mL; HYDROGEN PEROXIDE 0.125 mL/100 mL; WATER

Chlorhexidine Gluconate Alcohol Disinfectant-Precision

Purpose

Antiseptic-Antiseptic

Active Ingredient(s)

Alcohol 63%-77% v/v. Purpose: Antiseptic

Chlorhexidine Gluconate 0.45%-0.55% w/v Purpose: Antiseptic

Use

- surgical hand antiseptic: significantly reduces the number of micro-organisms on the hands and forearms prior to surgery or patient care
- healthcare personnel hand antiseptic: hand rub to help reduce bacteria that potentially can cause disease
- recommended for repeated use

USE

- healthcare personnel hand antiseptic: hand rub to help reduce bacteria that potentially can cause disease
- recommended for repeated use

Warnings

For external use only. Flammable. Keep away from heat or flame

Do not use

- in children less than 2 months of age
- on open skin wounds

When using this product keep out of eyes, ears, and mouth. In case of contact with eyes, rinse eyes thoroughly with water.
Stop use and ask a doctor if irritation or rash occurs. These may be signs of a serious condition.
Keep out of reach of children. If swallowed, get medical help or contact a Poison Control Center right away.

Stop use and ask a doctor if irritation or rash occurs. These may be signs of a serious condition.

Keep out of reach of children. If swallowed, get medical help or contact a Poison Control Center right away.

Directions

- Place enough product on hands to cover all surfaces. Rub hands together until dry.
- Supervise children under 6 years of age when using this product to avoid swallowing.

Other information

- Store between 15-30C (59-86F)
- Avoid freezing and excessive heat above 40C (104F)

Inactive ingredients

glycerin, hydrogen peroxide, purified water USP

Package Label - Principal Display Panel

50 mL NDC: 77919-001-01

60 mL NDC: 77919-001-02

100 mL NDC: 77919-001-03

250 mL NDC: 77919-001-04

500 mL NDC: 77919-001-05

1000 mL NDC: 77919-001-06